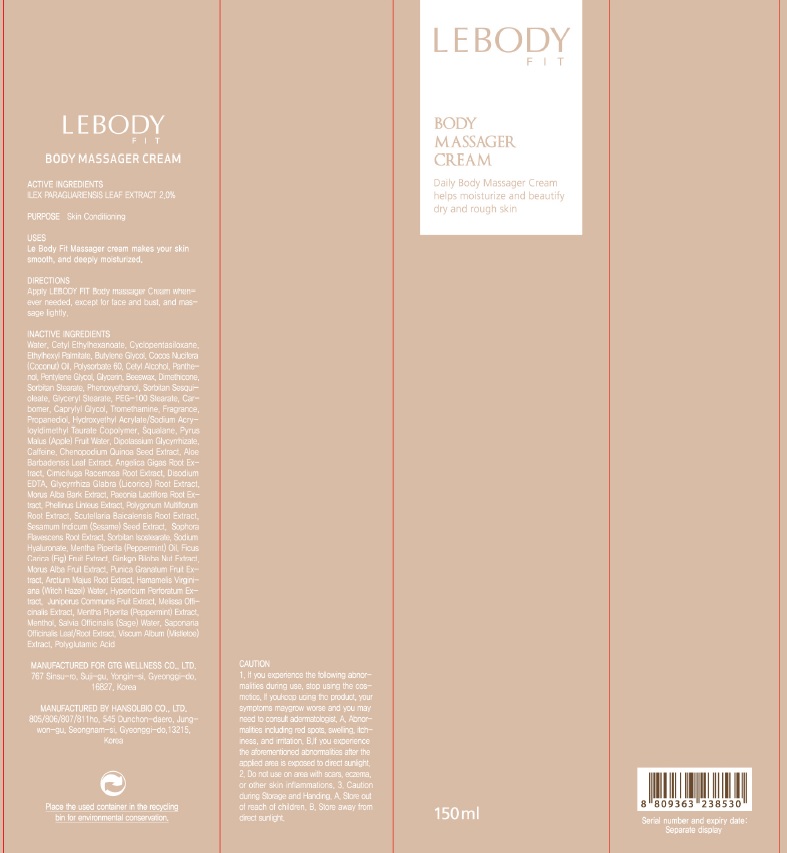 DRUG LABEL: LeBody Fit
NDC: 71080-0002 | Form: CREAM
Manufacturer: GTG Wellness Co., Ltd.
Category: otc | Type: HUMAN OTC DRUG LABEL
Date: 20171123

ACTIVE INGREDIENTS: ILEX PARAGUARIENSIS LEAF 3.0 g/150 mL
INACTIVE INGREDIENTS: Water; Cetyl Ethylhexanoate

ACTIVE INGREDIENT

Active ingredients: ILEX PARAGUARIENSIS LEAF EXTRACT 2.0%

INACTIVE INGREDIENT

Inactive ingredients:

Water, Cetyl Ethylhexanoate, Cyclopentasiloxane, Ethylhexyl Palmitate, Butylene Glycol, Cocos Nucifera (Coconut) Oil, Polysorbate 60, Cetyl Alcohol, Panthenol, Pentylene Glycol, Glycerin, Beeswax, Dimethicone, Sorbitan Stearate, Phenoxyethanol, Sorbitan Sesquioleate, Glyceryl Stearate, PEG-100 Stearate, Carbomer, Caprylyl Glycol, Tromethamine, Fragrance, Propanediol, Hydroxyethyl Acrylate/Sodium Acryloyldimethyl Taurate Copolymer, Squalane, Pyrus Malus (Apple) Fruit Water, Dipotassium Glycyrrhizate, Caffeine, Chenopodium Quinoa Seed Extract, Aloe Barbadensis Leaf Extract, Angelica Gigas Root Extract, Cimicifuga Racemosa Root Extract, Disodium EDTA, Glycyrrhiza Glabra (Licorice) Root Extract, Morus Alba Bark Extract, Paeonia Lactiflora Root Extract, Phellinus Linteus Extract, Polygonum Multiflorum Root Extract, Scutellaria Baicalensis Root Extract, Sesamum Indicum (Sesame) Seed Extract, Sophora Flavescens Root Extract, Sorbitan Isostearate, Sodium Hyaluronate, Mentha Piperita (Peppermint) Oil, Ficus Carica (Fig) Fruit Extract, Ginkgo Biloba Nut Extract, Morus Alba Fruit Extract, Punica Granatum Fruit Extract, Arctium Majus Root Extract, Hamamelis Virginiana (Witch Hazel) Water, Hypericum Perforatum Extract, Juniperus Communis Fruit Extract, Melissa Officinalis Extract, Mentha Piperita (Peppermint) Extract, Menthol, Salvia Officinalis (Sage) Water, Saponaria Officinalis Leaf/Root Extract, Viscum Album (Mistletoe) Extract, Polyglutamic Acid

PURPOSE

Purpose: Skin Conditioning

WARNINGS

Caution:

1. If you experience the following abnormalities during use, stop using the cosmetics. If you keep using the product, your symptoms may grow worse and you may need to consult a dermatologist.

A. Abnormalities including red spots, swelling, itchiness, and irritation.

B. If you experience the aforementioned abnormalities after the applied area is exposed to direct sunlight.

2. Do not use on area with scars, eczema, or other skin inflammations.

3. Caution during

A. Storage and Handing.Store out of reach of children.

B. Store away from direct sunlight.

KEEP OUT OF REACH OF CHILDREN

Store out of reach of children.

Uses

Le Body Fit Massager cream makes your skin smooth, and deeply moisturized.

Directions

Directions: Apply LEBODY FIT Body massager Cream whenever needed, except for face and bust, and massage lightly.